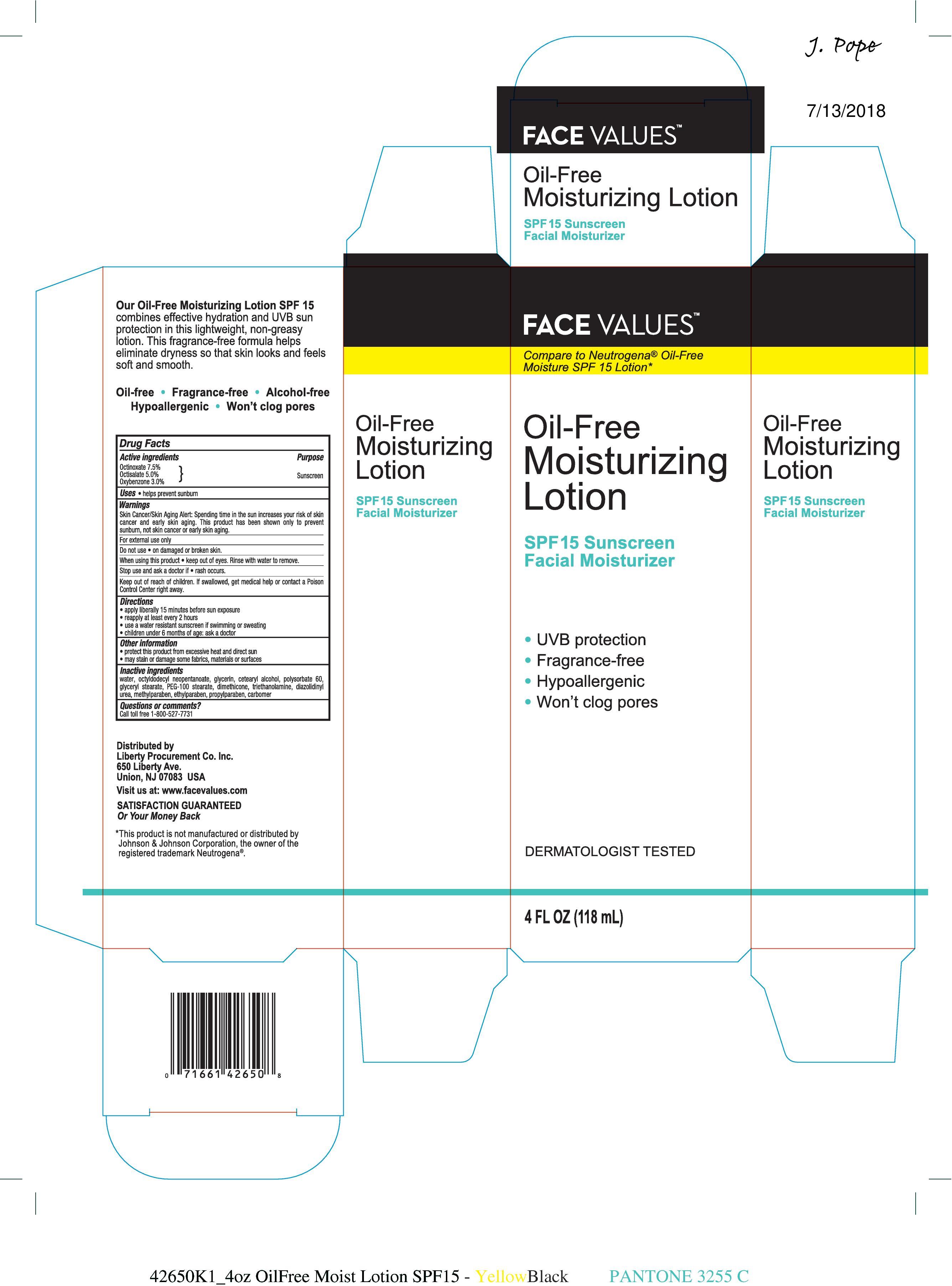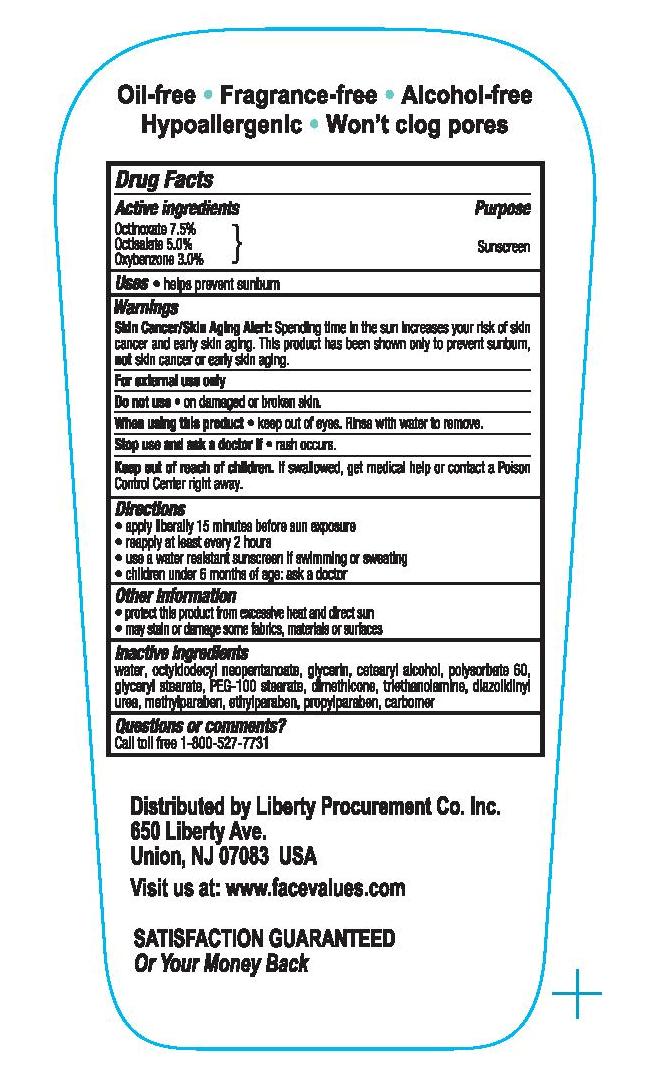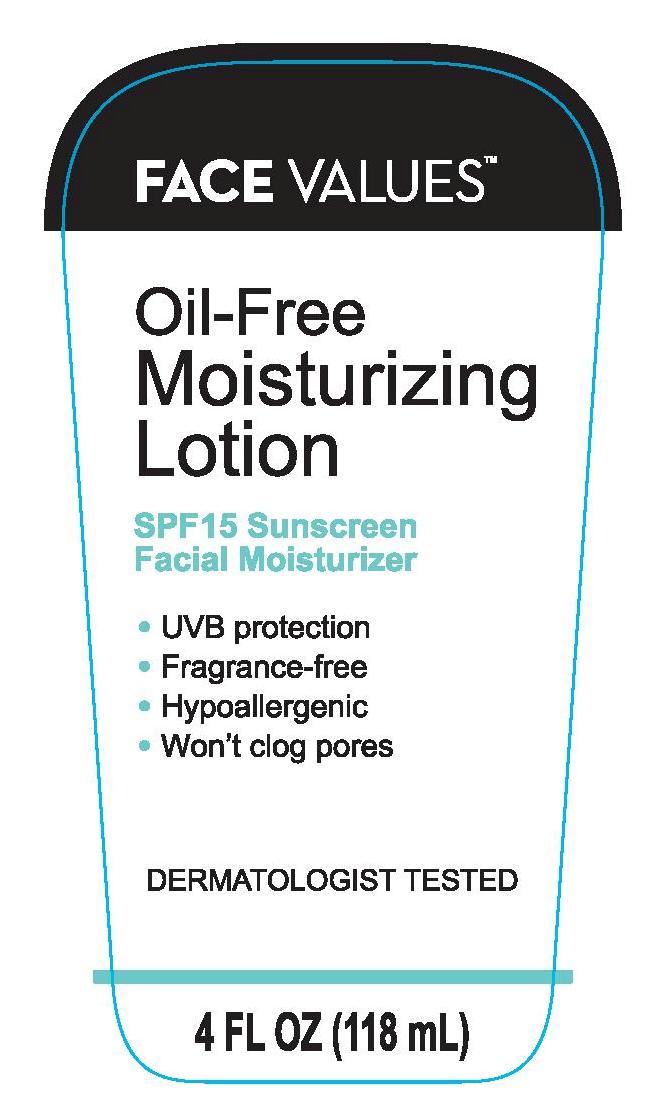 DRUG LABEL: FACE VALUES SPF 15 FACIAL MOISTURIZER
NDC: 63940-073 | Form: LOTION
Manufacturer: HARMON STORES, INC.
Category: otc | Type: HUMAN OTC DRUG LABEL
Date: 20241021

ACTIVE INGREDIENTS: OCTINOXATE 30 mg/1 mL; OCTISALATE 50 mg/1 mL; OXYBENZONE 30 mg/1 mL
INACTIVE INGREDIENTS: WATER; OCTYLDODECYL NEOPENTANOATE; GLYCERIN; CETOSTEARYL ALCOHOL; POLYSORBATE 60; GLYCERYL MONOSTEARATE; PEG-100 STEARATE; DIMETHICONE; TROLAMINE; DIAZOLIDINYL UREA; METHYLPARABEN; ETHYLPARABEN; PROPYLPARABEN; CARBOMER INTERPOLYMER TYPE A (ALLYL SUCROSE CROSSLINKED)

FACE VALUES OIL-FREE SPF 15 FACIAL MOISTURIZING LOTION

Active ingredients

Octinoxate 7.5%, Octisalate 5.0%, Oxybenzone 3.0%

Purpose

Sunscreen

Uses

- helps prevent sunburn

Warnings

Skin Cancer/Skin Aging Alert: Spending time in the sun increases your risk of skin cancer and early skin aging. This product has been shown only to prevent sunburn, not skin cancer or early skin aging.

For external use only

Do not use • on damaged or broken skin

When using this product • keep out of eyes. Rinse with water to remove.

Stop use and ask a doctor if • rash occurs

Keep out of reach of children. If product is swallowed, get medical help or contact a Poison Control Center right away.

Directions

- apply liberally 15 minutes before sun exposure
- reapply at least every 2 hours
- use a water resistant sunscreen if swimming or sweating
- children under 6 months of age: ask a doctor

Other information

- protect this product from excessive heat and direct sun
- may stain or damage some fabrics, materials or surfaces

Inactive ingredients

water, octyldodecyl neopentanoate, glycerin, cetearyl alcohol, polysorbate 60, glyceryl stearate, PEG-100 stearate, dimethicone, triethanolamine, diazolidinyl urea, methylparaben, ethylparaben, propylparaben, carbomer

Questions or comments?

Call toll free 1-800-527-7731

PACKAGE LABEL

FACE VALUES OIL-FREE SPF 15 MOISTURIZING LOTION

4 FL OZ (118mL)

NDC 63940-069-04

FACE VALUES OIL-FREE SPF 15 MOISTURIZING LOTION

BLISTER PACK

NDC 63940-069-05